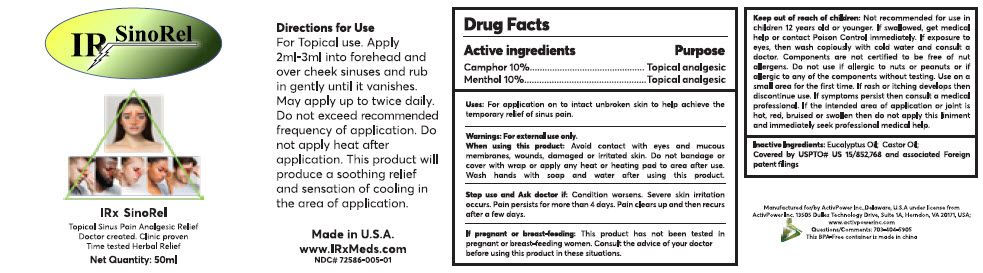 DRUG LABEL: IRxSinorel
NDC: 72586-005 | Form: LINIMENT
Manufacturer: ActivPower Inc.
Category: otc | Type: HUMAN OTC DRUG LABEL
Date: 20200702

ACTIVE INGREDIENTS: CAMPHOR (SYNTHETIC) 100 mg/1 mL; MENTHOL, UNSPECIFIED FORM 100 mg/1 mL
INACTIVE INGREDIENTS: EUCALYPTUS OIL; CASTOR OIL

IRxSinorel

Drug Facts

ACTIVE INGREDIENT

Active Ingredient | Purpose
Camphor 10% | Topical analgesic
Menthol 10% | Topical analgesic

Uses

For application on to intact unbroken skin to help achieve the temporary relief of sinus pain.

Warnings

For external use only.

When using this product

Avoid contact with eyes and mucous membranes, wounds, damaged or irritated skin. Do not bandage or cover with wrap or apply any heat or heating pad to area after use. Wash hands with soap and water after using this product.

Stop use and Ask doctor if

Condition worsens. Severe skin irritation occurs. Pain persists for more than 4 days. Pain clears up and then recurs after a few days.

If pregnant or breast-feeding

This product has not been tested in pregnant or breast-feeding women. Consult the advice of your doctor before using this product in these situations.

Keep out of reach of children

Not recommended for use in children 12 years old or younger. If swallowed, get medical help or contact Poison Control immediately. If exposure to eyes, then wash copiously with cold water and consult a doctor. Components are not certified to be free of nut allergens. Do not use if allergic to nuts or peanuts or if allergic to any of the components without testing. Use on a small area for the first time. If rash or itching develops then discontinue use. If symptoms persist then consult a medical professional. If the intended area of application or joint is hot, red, bruised or swollen then do not apply this liniment and immediately seek professional medical help.

Inactive Ingredients

Eucalyptus Oil; Castor Oil;

Directions for Use

For Topical use. Apply 2ml-3ml into forehead and over cheek sinuses and rub in gently until it vanishes. May apply up to twice daily. Do not exceed recommended frequency of application. Do not apply heat after application. This product will produce a soothing relief and sensation of cooling in the area of application.

Questions/Comments

703-404-5905

Manufactured for/by ActivPower Inc.,Delaware, U.S.A
under license from ActivPower Inc. 13505 Dulles
Technology Drive, Suite 1A, Herndon, VA 20171, USA;

PRINCIPAL DISPLAY PANEL - 50 ml Bottle Label

IRx SinoRel

Topical Sinus Pain Analgesic Relief
Doctor created. Clinic proven
Time tested Herbal Relief

Net Quantity: 50ml